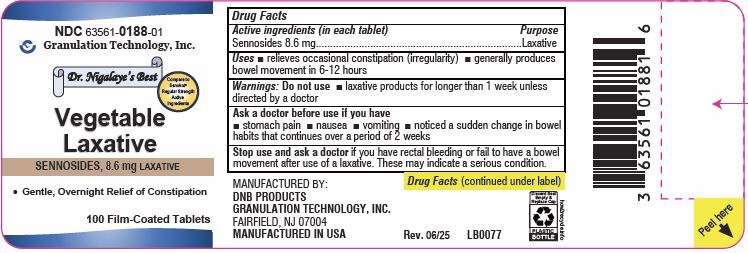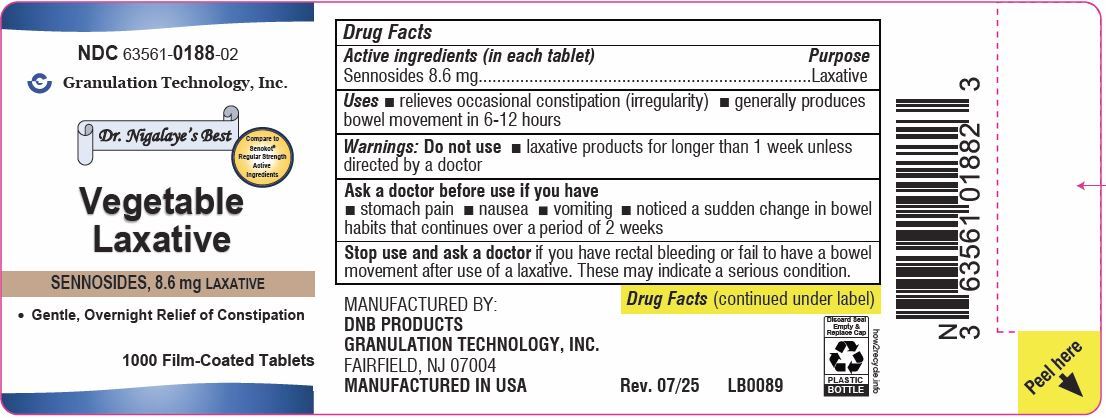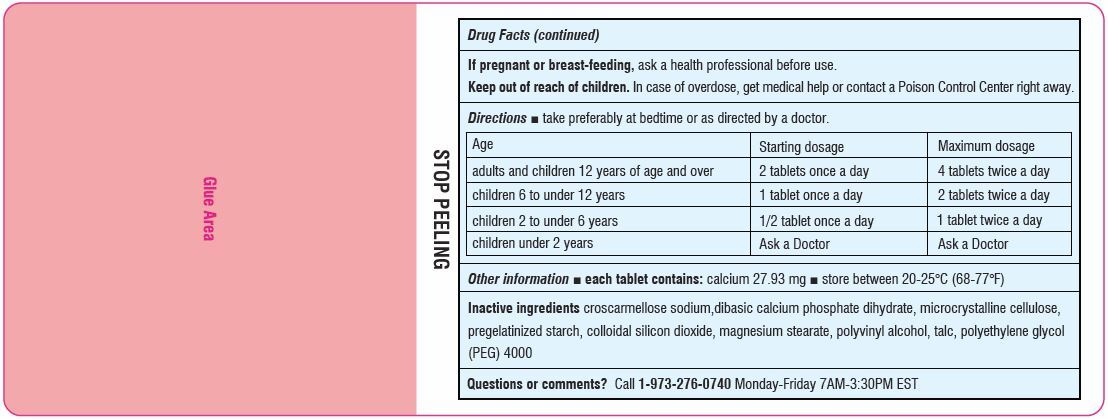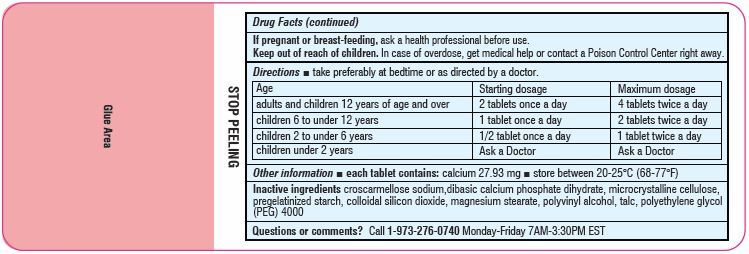 DRUG LABEL: Vegetable Laxative
NDC: 63561-0188 | Form: TABLET, FILM COATED
Manufacturer: Granulation Technology, Inc.
Category: otc | Type: HUMAN OTC DRUG LABEL
Date: 20250730

ACTIVE INGREDIENTS: SENNOSIDES 8.6 mg/1 1
INACTIVE INGREDIENTS: CELLULOSE, MICROCRYSTALLINE; STARCH, CORN; SILICON DIOXIDE; MAGNESIUM STEARATE; POLYVINYL ALCOHOL; POLYETHYLENE GLYCOL 4000; TALC; CROSCARMELLOSE SODIUM; DIBASIC CALCIUM PHOSPHATE DIHYDRATE

Vegetable Laxative
SENNOSIDES, 8.6 mg LAXATIVE

Active ingredients (in each tablet)

Sennosides                       8.6 mg

Purpose

Laxative

Uses

- Relieves occasional constipation (irregularity)
- Generally produces a bowel movement in 6-12 hours

Do not use

- Laxative products for longer than 1 week unless directed by a doctor

Ask a doctor before use if you have

- Stomach pain
- Nausea
- Vomiting
- Noticed a sudden change in bowel habits that continues over a period of 2 weeks

Stop using and ask a doctor if

you have rectal bleeding or fail to have a bowel movement after use of a laxative. These may indicate a serious condition.

If pregnant or breast-feeding,

ask a health professional before use.

Keep out of reach of children.

In case of overdose, get medical help or contact a Poison Control Center (1-800-222-1222) right away.

Directions

- Take preferably at bedtime or as directed by a doctor

age | starting dosage | maximum dosage
adults and children 12 years of age and over | 2 tablets once a day | 4 tablets twice a day
children 6 to under 12 years | 1 tablet once a day | 2 tablets twice a day
children 2 to under 6 years | 1/2 tablet once a day | 1 tablet twice a day
children under 2 years | ask a doctor | ask a doctor

Other information

- Each tablet contains:Calcium 27.93 mg
- Store between 20-25°C (68-77°F)

Inactive ingredients

croscarmellose sodium,dibasic calcium phosphate dihydrate, microcrystalline cellulose, pregelatinized starch, colloidal silicon dioxide, magnesium stearate, polyvinyl alcohol, polyethylene glycol (PEG) 4000, talc

Principal Display Panel

NDC 63561-0188-01

Vegetable Laxative Label

SENNOSIDES, 8.6 mg LAXATIVE

Compare to Senokot® Regular Strength Active Ingredients

100 Film-Coated Tablets

NDC 63561-0188-02

Vegetable Laxative Label

SENNOSIDES, 8.6 mg LAXATIVE

Compare to Senokot ® Regular Strength Active Ingredients

1000 Film-Coated Tablets